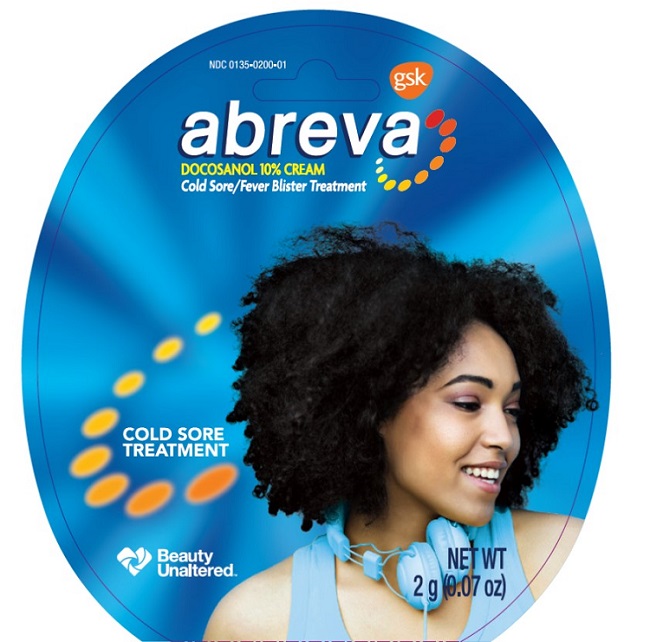 DRUG LABEL: ABREVA
NDC: 0135-0200 | Form: CREAM
Manufacturer: Haleon US Holdings LLC
Category: otc | Type: HUMAN OTC DRUG LABEL
Date: 20240620

ACTIVE INGREDIENTS: DOCOSANOL 100 mg/1 g
INACTIVE INGREDIENTS: BENZYL ALCOHOL; LIGHT MINERAL OIL; PROPYLENE GLYCOL; WATER; SUCROSE DISTEARATE; SUCROSE STEARATE

Drug Facts

Active ingredient

Docosanol 10%

Purpose

Cold sore/fever blister treatment

Uses

- treats cold sores/fever blisters on the face or lips
- shortens healing time and duration of symptoms:
  - tingling, pain, burning, and/or itching

Warnings

Allergy alert

This product may cause a severe allergic reaction. Symptoms
may include:

- hives
- facial swelling
- wheezing/difficulty breathing
- shock
- rash

If an allergic reaction occurs, stop use and seek medical help right away.

For external use only

Do not use

- if you are allergic to any ingredient in this product

When using this product

- apply only to affected areas
- do not use in or near the eyes
- avoid applying directly inside your mouth
- do not share this product with anyone. This may spread infection.

Stop use and ask a doctor if

- your cold sore gets worse or the cold sore is not healed within 10 days

Keep out of reach of children.

If swallowed, get medical help or contact a Poison Control Center right away.

Directions

- adults and children 12 years or over:
  - wash hands before and after applying cream
  - apply to affected area on face or lips at the first sign of cold sore/fever blister (tingle)
  - early treatment ensures the best results
  - rub in gently but completely
  - use 5 times a day until healed
- children under 12 years: ask a doctor

Other information

- store at 20o-25oC (68o-77oF)
- do not freeze

Inactive ingredients

benzyl alcohol, light mineral oil, propylene glycol, purified water, sucrose distearate, sucrose stearate

Questions or comments?

Call toll-free 1-877-709-3539

Additional information

*ABREVA contains the only OTC medicine approved by the FDA to shorten healing time and duration of symptoms.

Retain this insert for full product uses, directions and warnings.

If you are not completely satisfied, save receipt and remaining product, and call us at 1-877-709-3539.

Thank you for puchasing ABREVA.We hope that since ABREVA shortens the healing time of cold sores, it helps you look and feel better faster. Please follow insert directions for proper use and refer to the information below.

You are not alone

An estimated one-in-five Americans is affected by cold sores each year. Most people who experience them get two to three cold sore outbreaks each year. Just before and during an outbreak, the cold sore infection can be easily passed on to others. It is especially important to be aware of early warning signs that a cold sore is coming, and to be sure to avoid close physical contact when you have one.

Getting to the Root of the Problem

A blister, or cluster of blisters around your mouth, is caused by the cold sore virus. After the cold sore has healed, the virus stays dormant in your body but can be reactivated by everyday triggers like stress, sunlight, extreme hot or cold weather, colds and flu, lack of sleep, or menstruation.

The Sooner, the Better

A typical cold sore outbreak can last as long as seven to ten days. The sooner you begin using ABREVA, the more effective the medicine will be. So for best results, use ABREVA at the very start of the cold sore - when you feel the first sign of the tingle, redness, bump or itch.

Frequently Asked Questions:

How is ABREVA different from the Over-The-Counter cold sore remedies I have already been using?

Abreva contains 10% docosanol, the only FDA approved non-prescription ingredient that can actually shorten healing time and the duration of symptoms including tingling, pain, itching, and burning. The sooner you start using ABREVA, the sooner you can begin healing your cold sore. No other Over-The-Counter cold sore product heals your cold sore faster.

Who can use ABREVA?

Adults and children 12 years and over can use ABREVA.

How often can I apply ABREVA?

ABREVA should be used five times a day until the cold sore is healed. Apply it directly to the cold sore at the first sign of a tingle, redness, bump or itch for best results.

Can I apply cosmetics on top of ABREVA?

Yes, cosmetics such as lipstick may be applied over ABREVA. However, use a separate applicator, like a cotton swab, to apply cosmetics over an unhealed cold sore to avoid spreading the infection. For best results, remove any cosmetics prior to applying ABREVA.

For More Information:

Call us at 1-877-709-3539

Abreva
DOCOSANOL 10% CREAM
COLD SORE/FEVER BLISTER TREATMENT

Principal Display Panel

abreva

DOCOSANOL 10% CREAM

Cold Sore/Fever Blister Treatment

Cold Sore Treatment

Beauty Unaltered

NET WT

2g (0.07 oz)

1000771